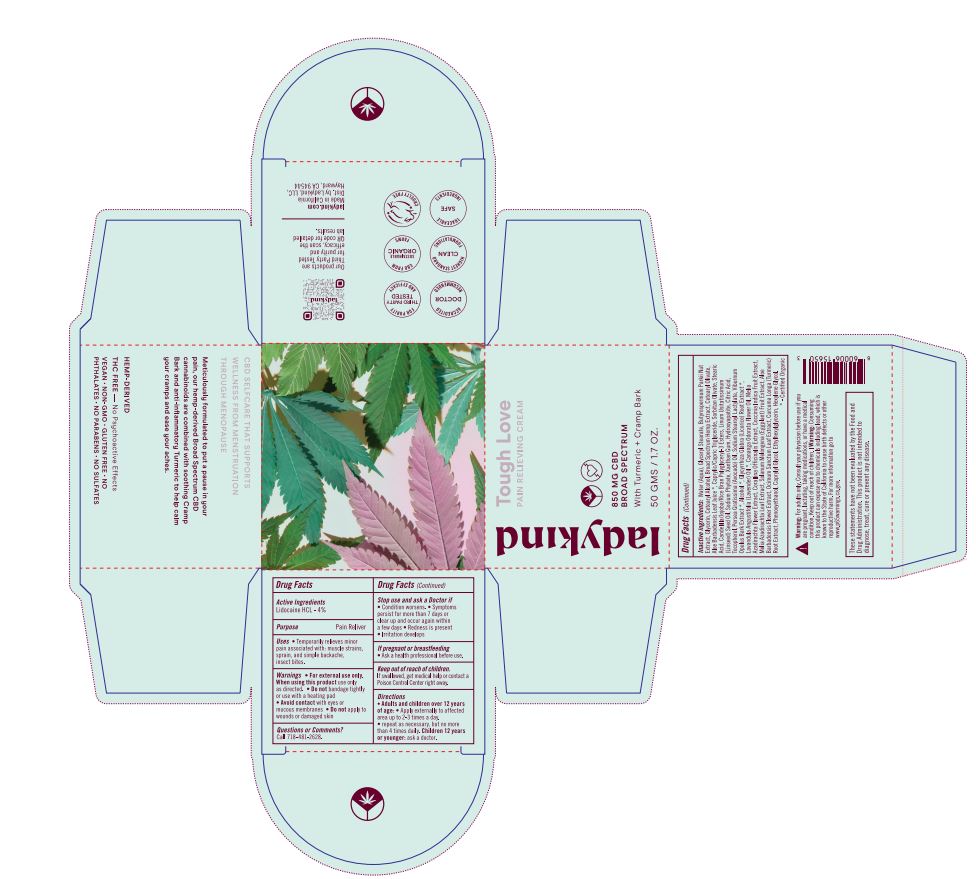 DRUG LABEL: Tough Love Pain Relieving
NDC: 62742-4222 | Form: CREAM
Manufacturer: Allure Labs
Category: otc | Type: HUMAN OTC DRUG LABEL
Date: 20241209

ACTIVE INGREDIENTS: LIDOCAINE 4 g/100 g
INACTIVE INGREDIENTS: RICE BRAN; STEARIC ACID; ETHYLHEXYLGLYCERIN; VIBURNUM OPULUS BARK; CANDELILLA WAX; ALCOHOL; WATER; SORBITAN OLIVATE; SHEANUT; LINSEED OIL; PHYTATE SODIUM; SODIUM STEAROYL LACTYLATE; PHENOXYETHANOL; CETEARYL OLIVATE; GLYCERYL MONOSTEARATE; GLYCYRRHIZA GLABRA; YLANG-YLANG OIL; AZADIRACHTA INDICA LEAF; ALOE VERA FLOWER; TURMERIC; XANTHAN GUM; TRIBASIC CALCIUM PHOSPHATE; TOCOPHEROL; AVOCADO OIL; LAVENDER OIL; EGGPLANT; CITRIC ACID MONOHYDRATE; GLYCERIN; HEXYLENE GLYCOL; JOJOBA OIL GLYCERETH-8 ESTERS; AZADIRACHTA INDICA FLOWER; MEDIUM-CHAIN TRIGLYCERIDES; CORALLINA OFFICINALIS; COCCINIA GRANDIS FRUIT; HOLY BASIL LEAF; CAPRYLYL GLYCOL; CETOSTEARYL ALCOHOL; ALOE VERA LEAF; CANNABIDIOL

Drug Facts

Active Ingredients

Lidocaine HCL 4 %

Purpose

Pain Reliver

Uses

Temporarily relieves minor pain associated with Muscle strains,sprain and simple backache,insect bites.

Warnings

For external use only

Do not uses

Do not apply to wounds or damaged skin

When using this Product use only as directed

do not bandage tightly or use with a heating pad

Stop uses

Condition Worsens

Symptoms persist for more than 7 days or clear up and occur again within a few days

Redness is present

Irritation develops

Keep out of reach of children

If swallowed get medical help or contact a poison control center right away

DOSAGE AND ADMINISTRATION

Direction

Adults and children over 12 years of age

apply externally to affected area up to 2-3 time a day.

repeat as necessary, but no more than 4 time daily.

children 12 year or younger ask a doctor

Other safety information and warning

Warning: For adults only. Consult your physician before use if you are pregnant, lactating, taking medications, or have a medical condition. Keep out of reach of children.

Warning: Consuming this product can expose you to chemicals including lead, which is known to the State of California to cause birth defects or other reproductive harm. For more information go to www.p65warnings.ca.gov.

These statements have not been evaluated by the Food and Drug Administration. This product is not intended to diagnose, treat, cure, or prevent any disease.

Inactive Ingredient

Water ((Aqua), Glyceryl stearate, Butyrospermum Parkii Nut Extract, glycerin, Ceteraryl Alcohol, Broad Spectrum Hemp Extract, Cetearyl Olivate, Aloe Barbadensis Leaf Juice, Caprylic/Capric Triglyceride, Sorbitan Olivate, stearic Acid, Candelilla/Jojoba/Rice Bran Polyglyceride-3Esters, Linum Usitatissimum(Linseed) Seed Oil, Sodium Phytate,Xanthan Gum, Hydroxyapatite, Citric Acid,Tocopherol,

Persea Gratissima (Avocado) Oil,Sodium Stearoyl Lactylate,Viburnum Opulus Bark Extract, Alcohol,Glycyrrhiza Glabra (Licorice) Root Extract, Lavandula Angustifolia (Lavender)Oil,Cananga Odorata Flower Oil, Melia Azadirachta Flower Extract,Corallina Officinalis Extract,Cocconia Indica Fruit Extract,Melia Azadirachta Leaf extract,Solanum Melongena (Eggplant) Fruit Extract, Aloe Barbadensis Flower Extract,Ocimum Sanctum Leaf Extract,Curcuma Longa (Turmeric) Root Extract, Phenoxyethanol,Caprylyl Glycol,Ethylhexylglycerin, Hexylene Glycol